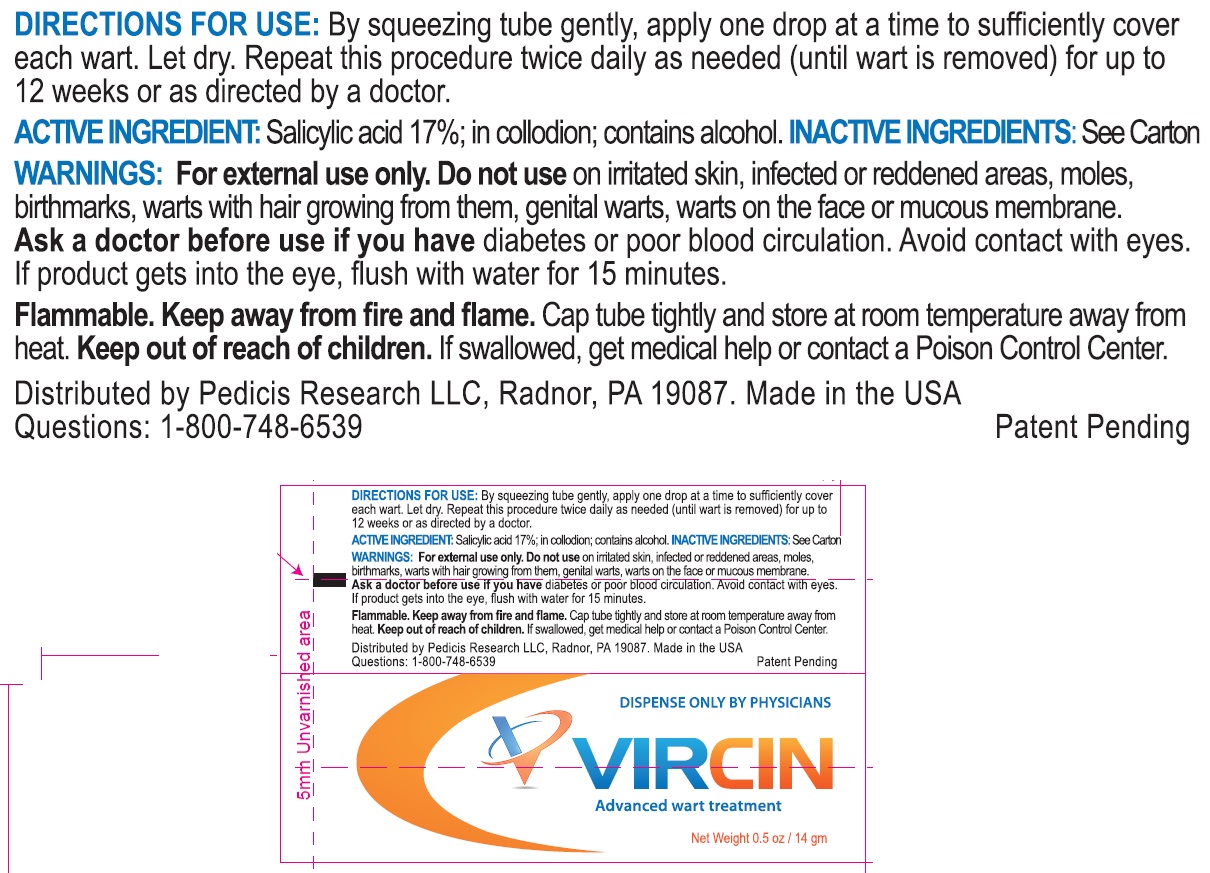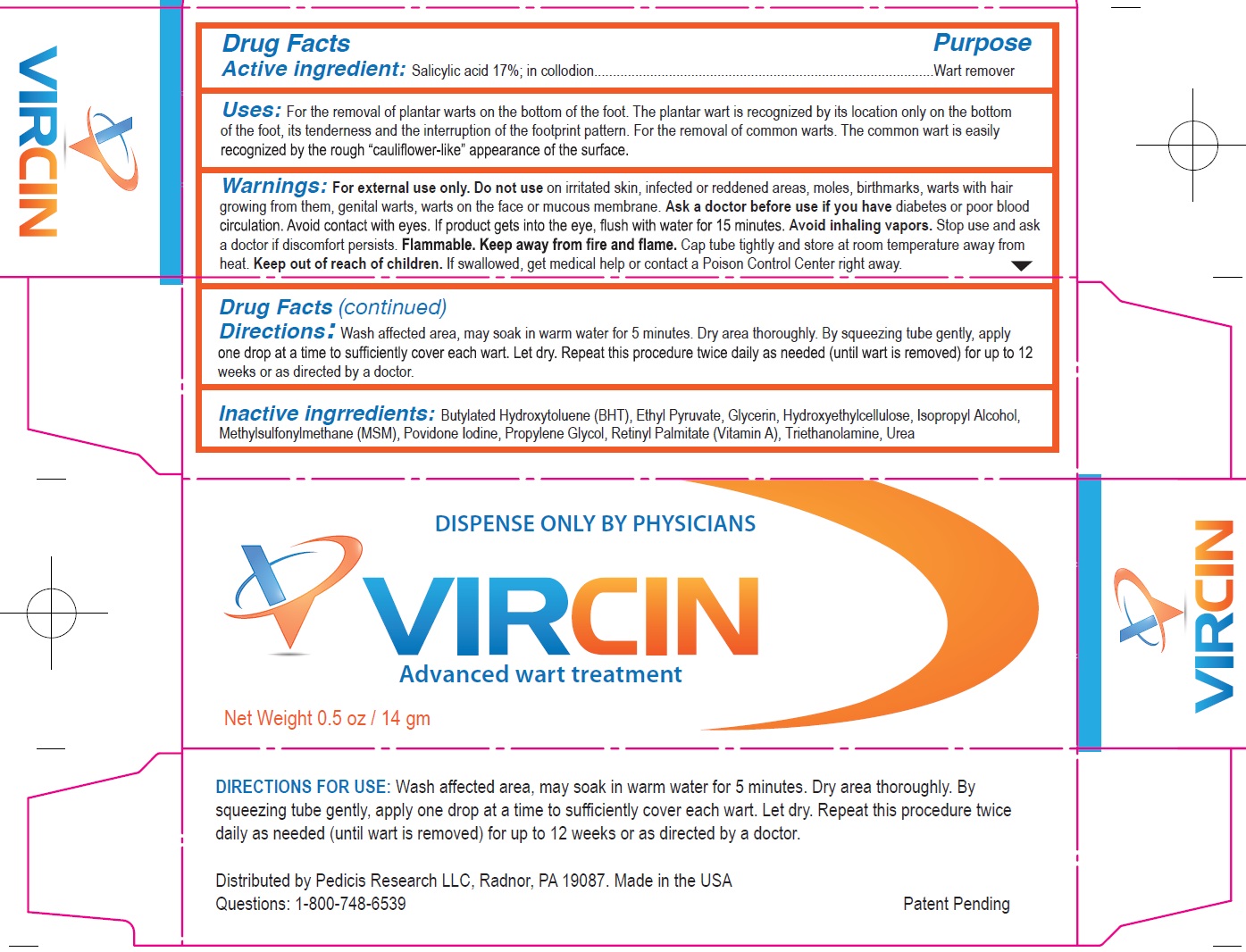 DRUG LABEL: VIRCIN Advanced wart treatment
NDC: 65121-397 | Form: CREAM
Manufacturer: Pure Source, LLC
Category: otc | Type: HUMAN OTC DRUG LABEL
Date: 20241218

ACTIVE INGREDIENTS: SALICYLIC ACID 17 g/100 g
INACTIVE INGREDIENTS: BUTYLATED HYDROXYTOLUENE; ETHYL PYRUVATE; GLYCERIN; POVIDONE-IODINE; PROPYLENE GLYCOL; TROLAMINE

VIRCIN Advanced wart treatment

Active Ingredient

Salicylic acid 17%; in collodion; contains alcohol

Purpose

Wart Remover

Uses:

For the removal of plantar warts on the bottom of the foot. The plantar wart is recognized by its location only on the bottom of the foot, its tenderness and the interruption of the footprint pattern. For the removal of common warts. The common wart is easily recognized by the rough “cauliflower-like” appearance of the surface.

Warnings

on irritated skin, infected or reddened areas, moles, birthmarks, warts with hair growing from them, genital warts, warts on the face or mucous membrane. diabetes or poor blood circulation. Avoid contact with eyes. If product gets into the eye, flush with water for 15 minutes. Stop use and ask a doctor if discomfort persists. Cap tube tightly and store at room temperature away from heat. For external use only. Do not use Ask a doctor before use if you have Avoid inhaling vapors. Flammable. Keep away from fire and flame.

Keep out of reach of children.

If swallowed, get medical help or contact a Poison Control Center right away.

Directions:

Wash affected area, may soak in warm water for 5 minutes. Dry area thoroughly. By squeezing tube gently, apply one drop at a time to sufficiently cover each wart. Let dry. Repeat this procedure twice daily as needed (until wart is removed) for up to 12 weeks or as directed by a doctor.

Inactive Ingredients:

BHT, Ethyl Pyruvate, Glycerin, Povidone Iodine, Propylene Glycol, Transcutol, Triethanolamine